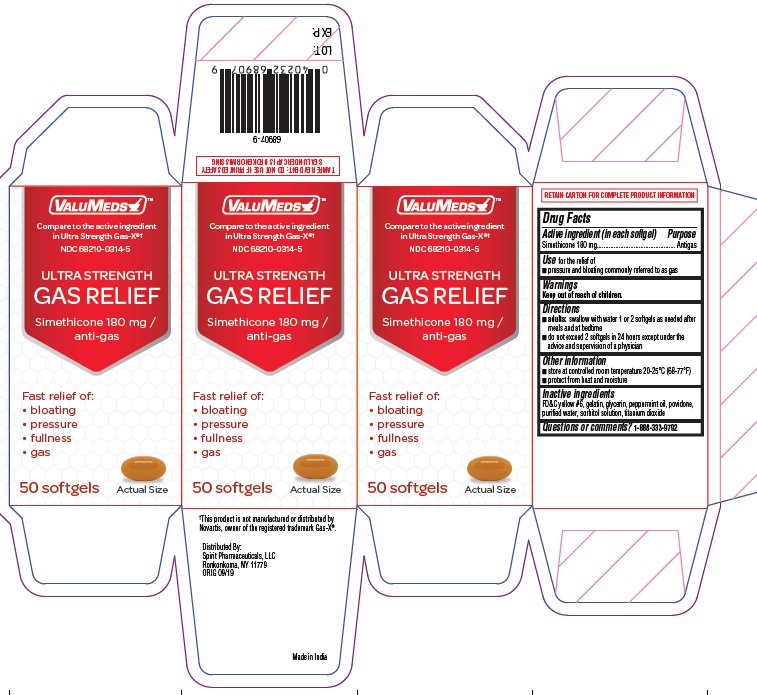 DRUG LABEL: Simethicone
NDC: 68210-0314 | Form: CAPSULE, GELATIN COATED
Manufacturer: Spirit Pharmaceuticals LLC
Category: otc | Type: HUMAN OTC DRUG LABEL
Date: 20241212

ACTIVE INGREDIENTS: DIMETHICONE 180 mg/1 1
INACTIVE INGREDIENTS: FD&C YELLOW NO. 6; GELATIN; GLYCERIN; PEPPERMINT OIL; WATER; SORBITOL SOLUTION; TITANIUM DIOXIDE

ULTRA STRENGTH GAS RELIEF

Drug Facts

Active ingredient (in each softgel)

Simethicone 180 mg

Purpose

Antigas

Use

for the relief of
■ pressure and bloating commonly referred to as gas

Warnings

Keep out of reach of children.

Keep out of reach of children.

Directions

■ adults: swallow with water 1 or 2 softgels as needed after
meals and at bedtime
■ do not exceed 2 softgels in 24 hours except under the
advice and supervision of a physician

Other information

■ store at controlled room temperature 20-25°C (68-77°F)
■ protect from heat and moisture

Inactive ingredients

FD&C yellow #6, gelatin, glycerin, peppermint oil, povidone, purified water, sorbitol solution, titanium dioxide

Questions or comments?

1-888-333-9792

PRINCIPAL DISPLAY PANEL

ULTRA STRANGTH

GAS RELIEF
Simethicone 180 mg /
anti-gas

Fast relief of:
• bloating
• pressure
• fullness
• gas

50 SOFTGELS